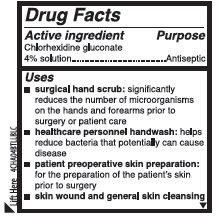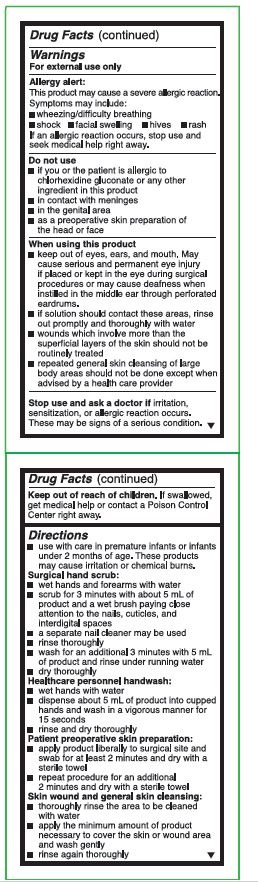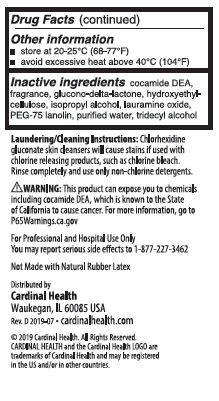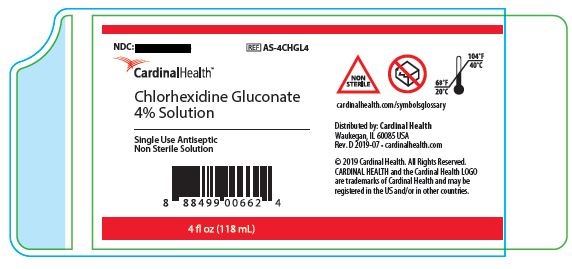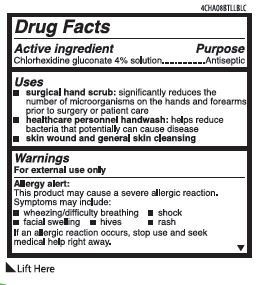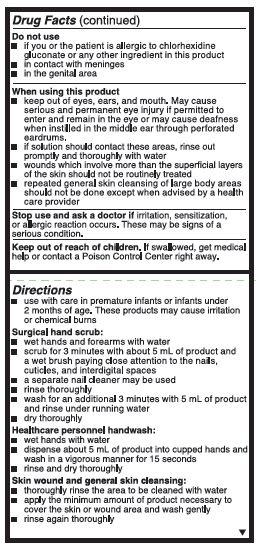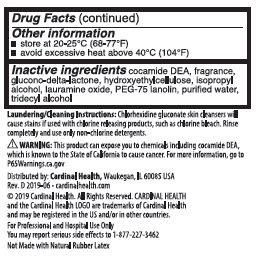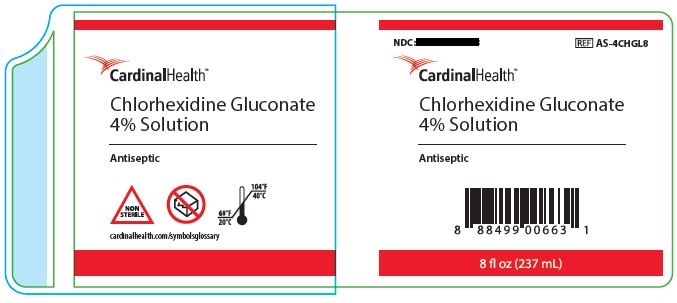 DRUG LABEL: Cardinal Health
NDC: 0116-0061 | Form: LIQUID
Manufacturer: Xttrium Laboratories, Inc.
Category: otc | Type: HUMAN OTC DRUG LABEL
Date: 20251208

ACTIVE INGREDIENTS: CHLORHEXIDINE GLUCONATE 4 g/100 mL
INACTIVE INGREDIENTS: GLUCONOLACTONE; PEG-75 LANOLIN; TRIDECYL ALCOHOL; COCO DIETHANOLAMIDE; HYDROXYETHYL CELLULOSE (2000 CPS AT 1%); ISOPROPYL ALCOHOL; LAURAMINE OXIDE; WATER

XTT Cardinal Health 4%
COMP 8oz

ACTIVE INGREDIENT

Chlorhexidine gluconate 4% Solution

Purpose

Antiseptic

Uses

- surgical hand scrub: significantly reduces the number of microorganisms on the hands and forearms prior to surgery or patient care
- healthcare personnel handwash: helps reduce bacteria that potentially can cause disease
- patient preoperative skin preparation: for the preparation of the patient's skin prior to surgery
- skin wound and general cleansing

Warnings

For external use only

Allergy alert:

This product may cause a severe allergic reation. Symptoms may include:

- wheezing/difficulty breathing
- shock
- facial swelling
- hives
- rash

If an allergic reaction occurs, stop use and seek medical help right away.

Do not use

- if you or the patient is allergic to chlorhexidine gluconate or any other ingredient in this product
- in contact with meninges
- in the genital area
- as a preoperative skin preparation of the head or face

When using this product

- keep out of eyes, ears, and mouth. May cause serious and permanent eye injury if placed or kept in the eye during surgical procedures or may cause deafness when instilled in the middle ear through perforated eardrums.
- if solution should contact these areas, rinse out promptly and thoroughly with water
- wound which involve more than the superficial layers of the skin should not be routinely treated
- repeated general skin cleansing of large body areas should not be done except when advised by a health care provider

Stop use and ask a doctor

if irritation, sensitization, or allergic reaction occurs. These may be signs of a serious condition.

Keep out of reach of children

If swallowed, get medical help or contact a Poison Control Center right away.

Direction

- use with care in premature infants or infants under 2 months of age. These products may cause irritation or chemical burns.

Surgical hand scrub:

- wet hands and forearms with water.
- scrub for 3 minutes with about 5 mL of product and a wet brush paying close attention to the nails, cuticles, and interdigital spaces
- a separate nail cleaner may be used
- rinse throughly
- wash for an additional 3 minutes with 5 mL of product and rinse under running water
- dry thoroughly

Healthcare personnel handwash:

- wet hands with water
- dispense about 5 mL of product into cupped hands and wash in a vigorous manner for 15 seconds
- rinse and dry thoroughly

Patient preoperative skin preparation:

- apply product liberally to surgical site and swab for at least 2 minutes and dry with a sterile towel
- repeat procecedure for an additional 2 minutes and dry with a sterile towel

Skin wound and general skin cleansing:

- thoroughly rinse the area to be cleaned with water
- apply the minimum amount of product necessary to cover the skin or wound area and wash gently
- rinse again thoroughly

other information

- store at 20-25 C (68-77 F)
- avoid excessive heat above 40 C (104 F)

Inactive ingredients

cocamide DEA, fragrance, glucono-delta-lactone, hydroxyethylcellulose, isopropyl alcohol, lauramine oxide, PEG-75 lanolin, purified water, tridecyl alcohol

OTHER SAFETY INFORMATION

Laundering/Cleaning Instructions: Chlorhexidine gluconate skin cleansers will cause stains if used with chlorine releasing products, such as chlorine bleach. Rinse completely and use only non-chlorine detergents.

WARNING: This product can expose you to chemicals including cocamide DEA, which is known to the State of California to cause cancer. For more informationm, go to P65Warnings.ca.gov

For Professional and Hospital Use Only

You may report serious side effects to 1-877-227-3642

Not Made with Natural Rubber Latex

Distributed by

Cardinal Health

Waukegan, IL 60085 USA

Rev. D 2019-07 • cardinalhealth.com

©2019 Cardinal Health. All Rights Reserved.

CARDINAL HEALTH and the Cardinal Health LOGO are

trademarks of Cardinal Health and may be registered

in the US and/or in other countries.

Package Label

NDC: 63517-061-04

AS-4CHGL4

Cardinal Health

Chlorhexidine Gluconate 4% Solution

Single-Use Antiseptic

Non Sterile Solution

4 fl oz (118mL)

NDC: 63517-061-08

AS-4CHGL8

Cardinal Health

Chlorhexidine Gluconate 4% Solution

Antiseptic

8 fl oz (237 mL)